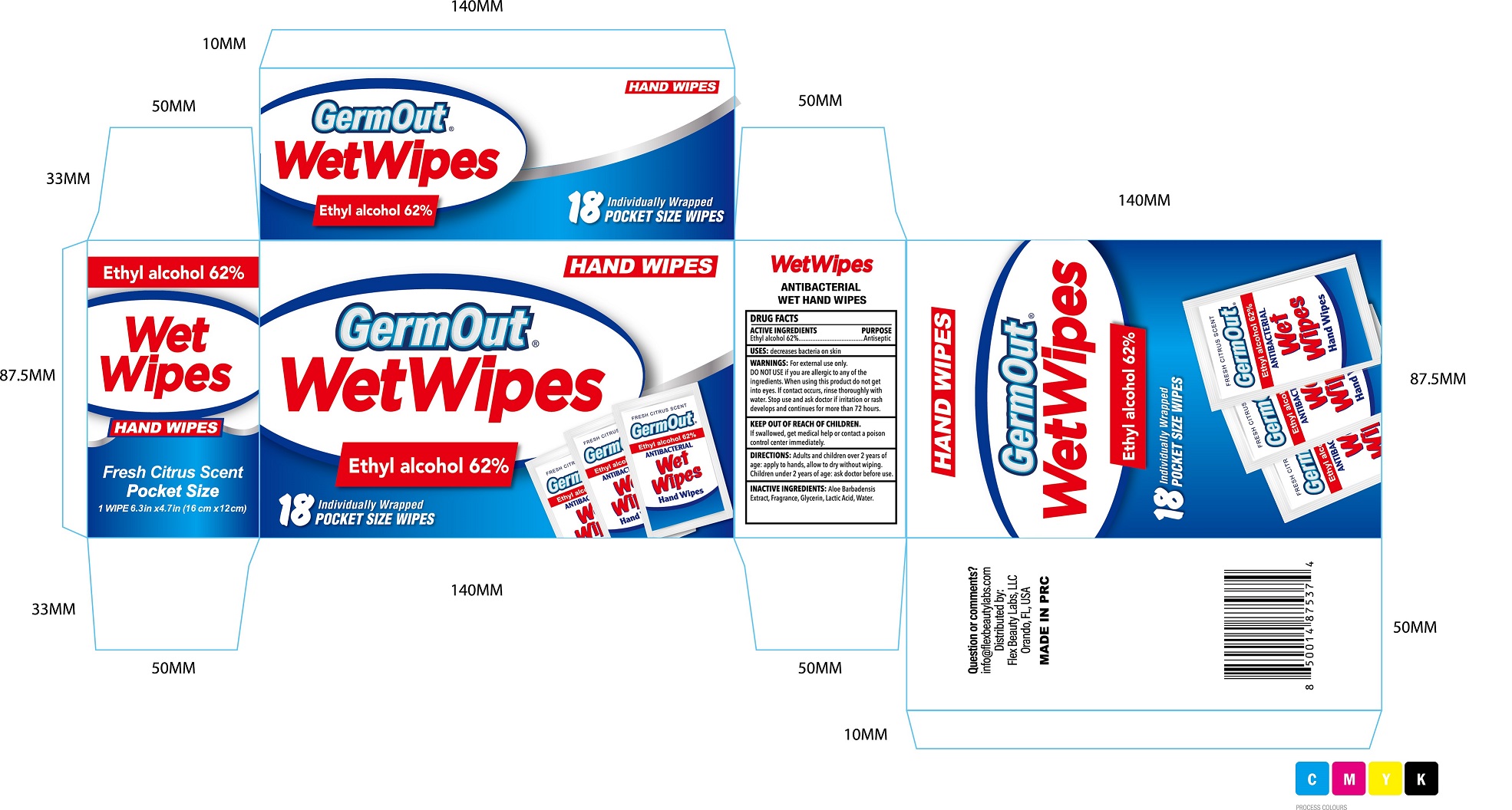 DRUG LABEL: Antiseptic Wipes
NDC: 72308-029 | Form: CLOTH
Manufacturer: Flex Beauty Labs
Category: otc | Type: HUMAN OTC DRUG LABEL
Date: 20200804

ACTIVE INGREDIENTS: ALCOHOL 62 mg/100 mg
INACTIVE INGREDIENTS: WATER; GLYCERIN; ALOE VERA LEAF; LACTIC ACID, UNSPECIFIED FORM

Germ Out Wet Wipes Alcohol WIPES

Active ingredients

Ethyl Alcohol 62%........ Antiseptic

Purpose

Antiseptic

Use

Decresases bacteria on skin

Warnings

For external use only

Do not use if you are allegic to any of the ingredients.

When using this product do not use in or near eyes.

In cases of contact, rinse eyes thoroughly with water.

Stop use and ask a doctor if irritation or redness develops and continues for more than 72 hours.

Keep out of reach of children.

If swallowed, get medical help or contact a Poison Control Center right away

Directions:

- Adults and children over 2 yeas of age:Apply to hands. Allow to dry without wioing.
- Children under 2 year of age:ask doctor before use

Inactive ingredients

Aloe barbadensis Extract, Fragrance, Glycerin, Lactic Acid, Water